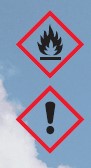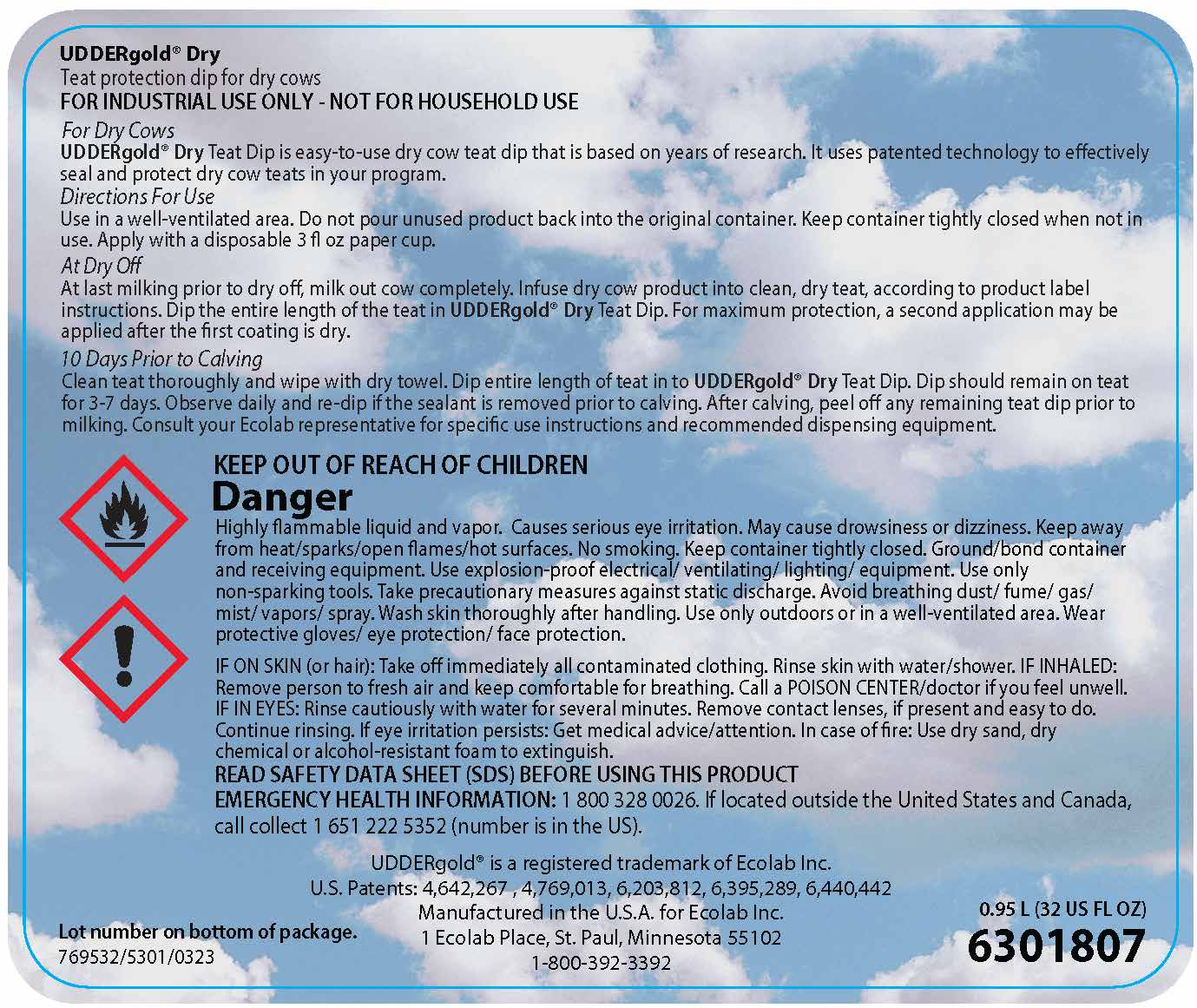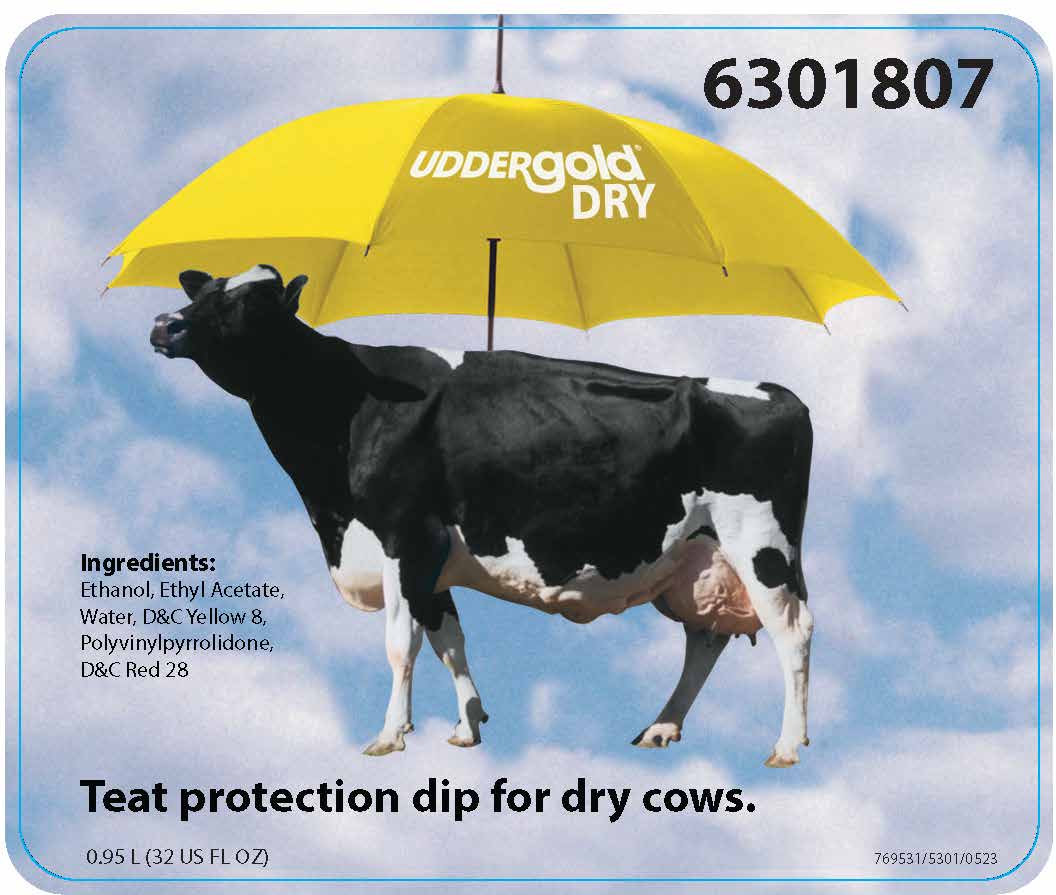 DRUG LABEL: UDDERgold Dry
NDC: 47593-852 | Form: Solution
Manufacturer: Ecolab Inc.
Category: animal | Type: OTC ANIMAL DRUG LABEL
Date: 20240124

ACTIVE INGREDIENTS: POVIDONE, UNSPECIFIED 0.910 g/1 L
INACTIVE INGREDIENTS: Alcohol; ETHYL ACETATE; water; FLUORESCEIN; D&C RED NO. 28

WARNINGS AND PRECAUTIONS

UDDERgold® DRY

Ingredients: Ethanol, Ethyl Acetate,
Water, D&C Yellow 8,
Polyvinylpyrrolidone,
D&C Red 28

Teat protection dip for dry cows.

0.95 L (32 US FL OZ)

INSTRUCTIONS FOR USE

UDDERgold® Dry
Teat protection dip for dry cows
FOR INDUSTRIAL USE ONLY - NOT FOR HOUSEHOLD USE
For Dry Cows
UDDERgold® Dry Teat Dip is easy-to-use dry cow teat dip that is based on years of research. It uses patented technology to effectively seal and protect dry cow teats in your program.

DOSAGE AND ADMINISTRATION

Directions For Use
Use in a well-ventilated area. Do not pour unused product back into the original container. Keep container tightly closed when not in
use. Apply with a disposable 3 fl oz paper cup.
At Dry Off
At last milking prior to dry off, milk out cow completely. Infuse dry cow product into clean, dry teat, according to product label
instructions. Dip the entire length of the teat in UDDERgold® Dry Teat Dip. For maximum protection, a second application may be
applied after the first coating is dry.
10 Days Prior to Calving
Clean teat thoroughly and wipe with dry towel. Dip entire length of teat in to UDDERgold® Dry Teat Dip. Dip should remain on teat
for 3-7 days. Observe daily and re-dip if the sealant is removed prior to calving. After calving, peel off any remaining teat dip prior to
milking. Consult your Ecolab representative for specific use instructions and recommended dispensing equipment.

KEEP OUT OF REACH OF CHILDREN

OTHER SAFETY INFORMATION

IF ON SKIN (or hair): Take off immediately all contaminated clothing. Rinse skin with water/shower. IF INHALED:
Remove person to fresh air and keep comfortable for breathing. Call a POISON CENTER/doctor if you feel unwell.
IF IN EYES: Rinse cautiously with water for several minutes. Remove contact lenses, if present and easy to do.
Continue rinsing. If eye irritation persists: Get medical advice/attention. In case of fire: Use dry sand, dry
chemical or alcohol-resistant foam to extinguish.
READ SAFETY DATA SHEET (SDS) BEFORE USING THIS PRODUCT
EMERGENCY HEALTH INFORMATION: 1 800 328 0026. If located outside the United States and Canada,
call collect 1 651 222 5352 (number is in the US).

UDDERgold® is a registered trademark of Ecolab Inc.
U.S. Patents: 4,642,267 , 4,769,013, 6,203,812, 6,395,289, 6,440,442
Manufactured in the U.S.A. for Ecolab Inc.
1 Ecolab Place, St. Paul, Minnesota 55102
1-800-392-3392

Lot number on bottom of package.

0.95 L (32 US FL OZ)